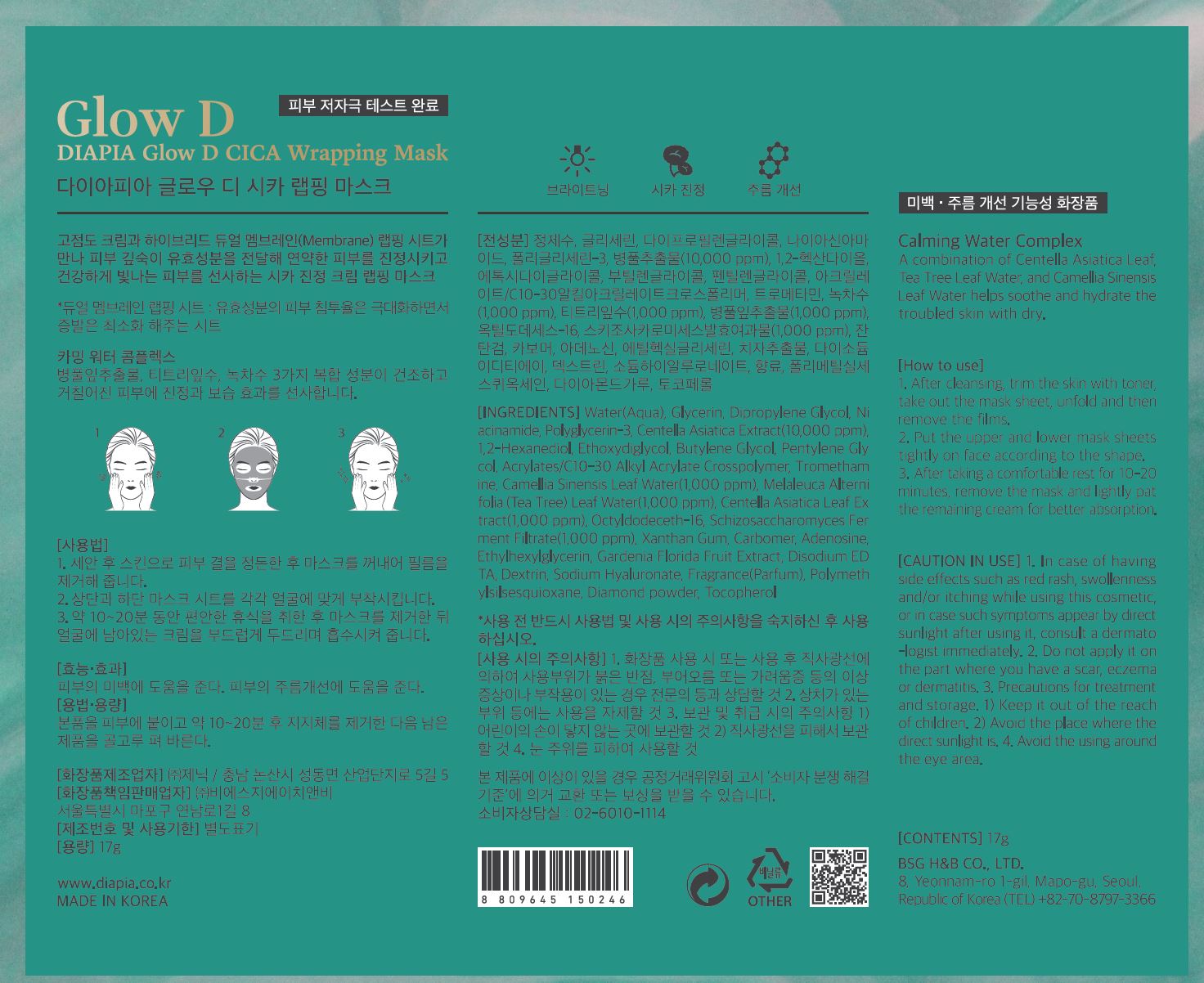 DRUG LABEL: DIAPIA Glow D CICA Wrapping Mask
NDC: 71857-0018 | Form: LIQUID
Manufacturer: BSG H & B Co., Ltd.
Category: otc | Type: HUMAN OTC DRUG LABEL
Date: 20211210

ACTIVE INGREDIENTS: ADENOSINE 0.04 g/100 g; NIACINAMIDE 2 g/100 g
INACTIVE INGREDIENTS: WATER

Drug Facts

ACTIVE INGREDIENT

Niacinamide

adenosine

INACTIVE INGREDIENT

Water(Aqua)
Glycerin
Dipropylene Glycol
Polyglycerin-3
1,2-Hexanediol
Ethoxydiglycol
Butylene Glycol
Pentylene Glycol
Acrylates/C10-30 Alkyl Acrylate Crosspolymer
Tromethamine
Camellia Sinensis Leaf Water
Melaleuca Alternifolia (Tea Tree) Leaf Water
Octyldodeceth-16
Schizosaccharomyces Ferment Filtrate
Centella Asiatica Extract
Xanthan Gum
Carbomer
Ethylhexylglycerin
Gardenia Florida Fruit Extract
Disodium EDTA
Dextrin
Sodium Hyaluronate
Fragrance(Parfum)
Polymethylsilsesquioxane
Centella Asiatica Leaf Extract
Diamond powder
Tocopherol

PURPOSE

Brightening, anti wrinkle care

keep out of reach of the children

INDICATIONS AND USAGE

after cleansing trim the skin with toner, take out the mask sheet, unfuld and then remove the films

put the upper and lower mask sheets tightly on face according to the shape

after taking a comfortable rest for 10-20 minutes, remove the mask and lightly pat the remaining cream for better absorption

WARNINGS

1.Keep out of reach of children.

2.Store in a cool, dry place and avoid direct sunlight.

3.If abnormal symptoms occur after use, stop use and consult with a skin specialist.

DOSAGE AND ADMINISTRATION

for external use only